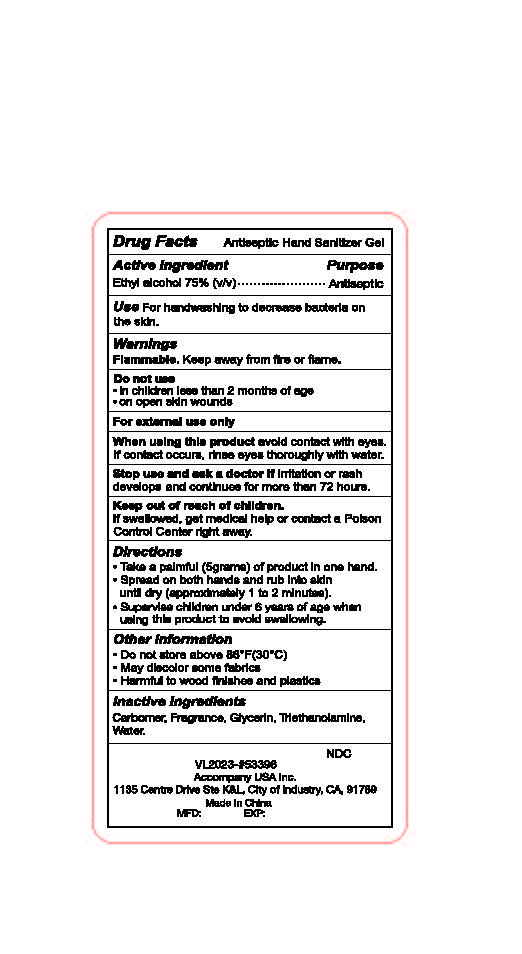 DRUG LABEL: hand sanitizer
NDC: 73788-104 | Form: GEL
Manufacturer: Hangzhou Huiji Biotechnology Co., Ltd.
Category: otc | Type: HUMAN OTC DRUG LABEL
Date: 20220224

ACTIVE INGREDIENTS: ALCOHOL 75 mL/100 mL
INACTIVE INGREDIENTS: TROLAMINE; CARBOMER 934; WATER; GLYCERIN

73788-104 75% alcohol Accompany Antiseptic Hand Sanitizer Gel

Active Ingredient

Ethyl Alcohol 75%

Purpose

Antiseptic

Use

For handwashing to decrease bacteria on
the skin.

WARNINGS

Flammable. Keep away from fire or flame.
Do not use
●in children less than 2 months of age
●on open skin wounds
For external use only
When using this product avoid contact with eyes.
If contact occurs, rinse eyes thoroughly with water.
Stop use and ask a doctor if irritation or rash
develops and continues for more than 72 hours.

keep out of reach of children

if swallowed, get medical help or contact a Poison Control Center right away.

Directions

●Take a palmful (5grams) of product in one hand.
●Spread on both hands and rub into skin
until dry (approximately 1 to 2 minutes).
●Supervise children under 6 years of age when
using this product to avoid swallowing.

Other Information

1 Do not store above 105°F
1 May discolor some fabrics

Inactive ingredients

Carbomer, Fragrance, Glycerin, Triethanolamine,
Water,